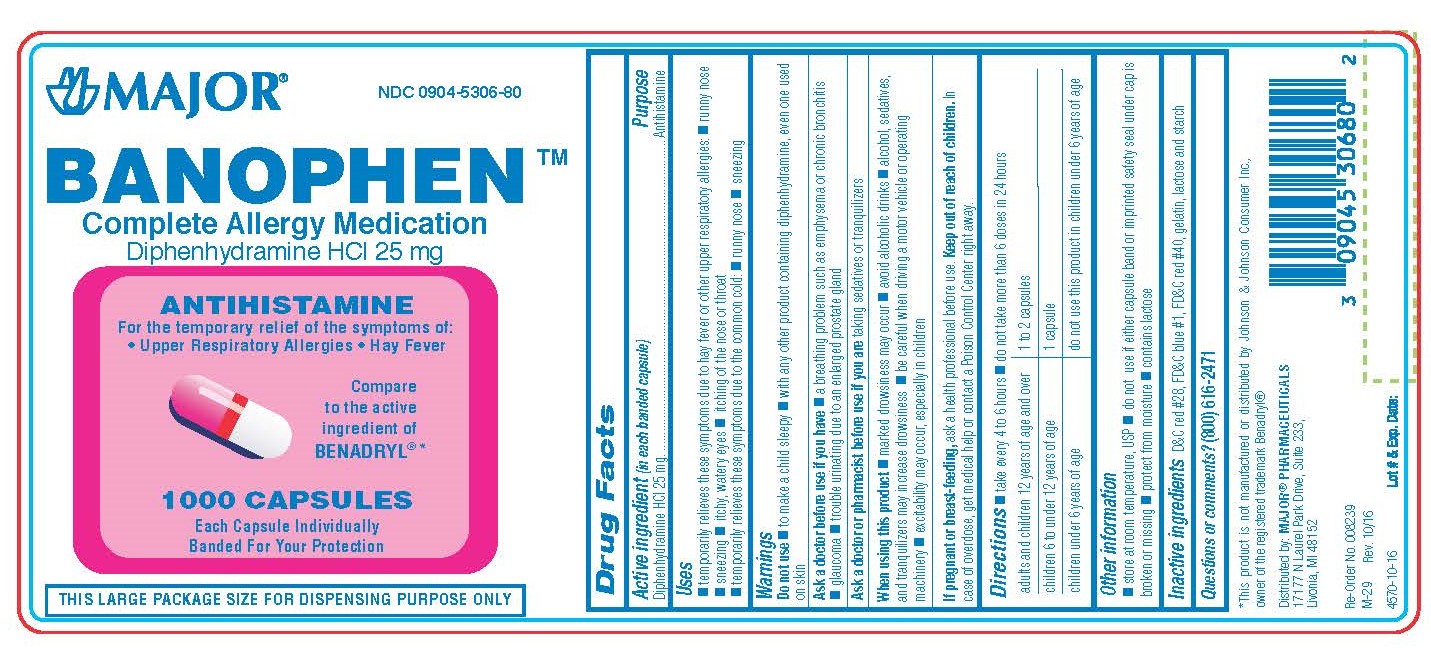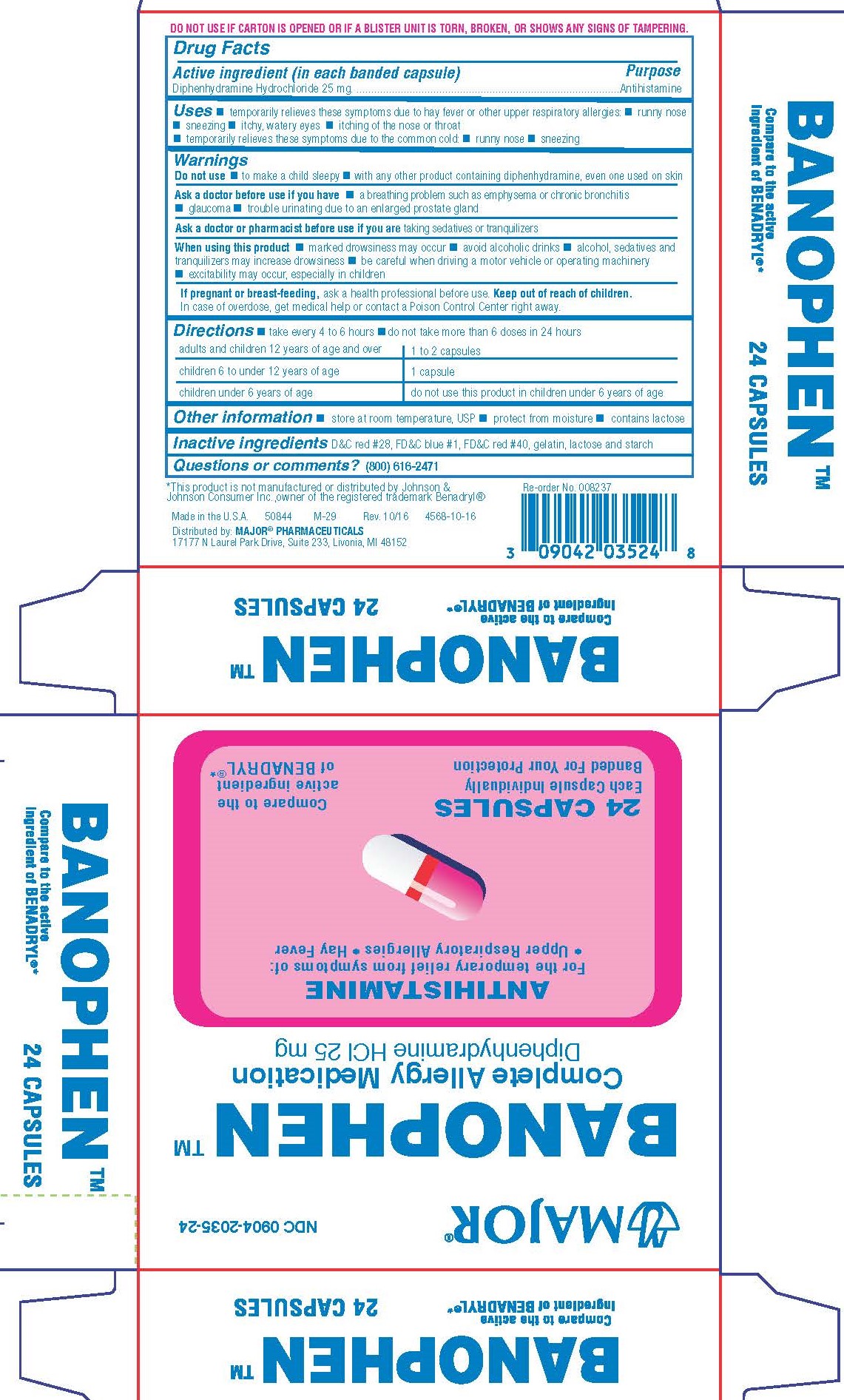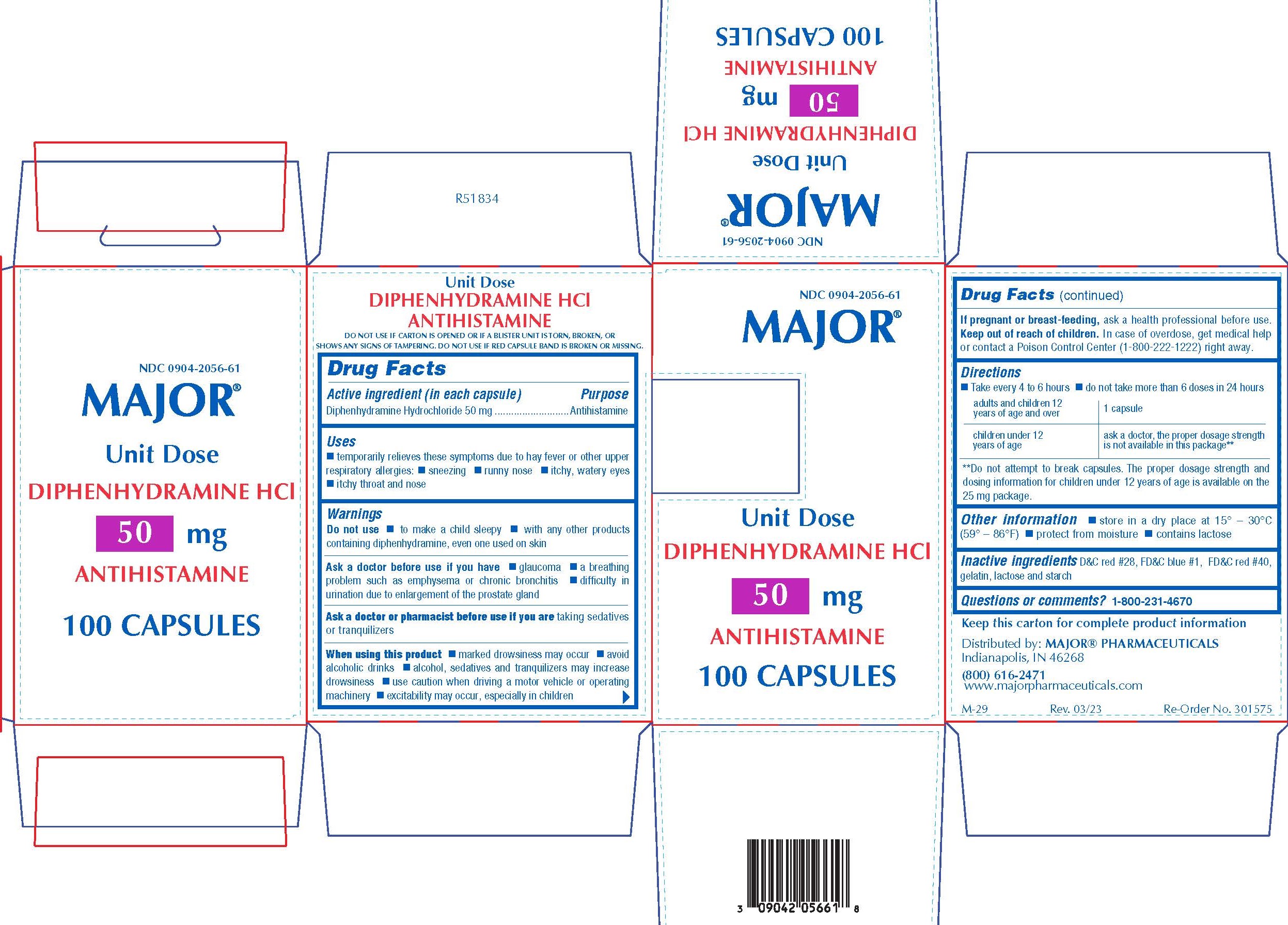 DRUG LABEL: Diphenhydramine Hydrochloride
NDC: 0904-5306 | Form: CAPSULE
Manufacturer: Major Pharmaceuticals
Category: otc | Type: HUMAN OTC DRUG LABEL
Date: 20260220

ACTIVE INGREDIENTS: DIPHENHYDRAMINE HYDROCHLORIDE 25 mg/1 1
INACTIVE INGREDIENTS: D&C RED NO. 28; FD&C BLUE NO. 1; FD&C RED NO. 40; GELATIN; LACTOSE MONOHYDRATE; STARCH, CORN

0835&0836(box unit)-Major

Active Ingredient (in each banded capsule)

Diphenhydramine HCl… 25 mg

Diphenhydramine HCl… 50 mg

Purpose

Antihistamine

Use

25 MG

- Temporarily relieves these symptoms due to hay fever or other upper respiratory allergies:
  - runny nose
  - sneezing
  - itchy, watery eyes
  - itchy throat and nose
- Temporarily relieves these symptoms due to the common cold:
  - runny nose
  - sneezing

50 MG

- Temporarily relieves these symptoms due to hay fever or other upper respiratory allergies and common cold
  - sneezing
  - runny nose
  - itchy, watery eyes
  - itchy throat and nose

WARNINGS

Do not use

25 MG

- to make a child sleepy
- with any other product containing diphenhydramine, even one used on skin

50 MG

- to make a child sleepy
- with any other product containing diphenhydramine, including one applied topically

Ask a doctor before use if you have

25 MG

- a breathing problem such as emphysema or chronic bronchitis
- glaucoma
- trouble urinating due to an enlarged prostate gland

50 MG

- glaucoma
- a breathing problem such as emphysema or chronic bronchitis
- difficulty in urination due to enlargement of the prostate gland

Ask a doctor or pharmacist

before use if you are taking sedatives or tranquilizers

When using this product

- marked drowsiness may occur
- avoid alcoholic drinks
- alcohol, sedatives, and tranquilizers may increase drowsiness
- be careful when driving a motor vehicle or operating machinery
- excitability may occur, especially in children

If pregnant or breast-feeding

ask a health professional before use.

KEEP OUT OF REACH OF CHILDREN

In case of overdose, get medical help or contact a Poison Control Center right away.

Directions

- Take every 4-6 hours
- Do not take more than 6 doses in 24 hours

25 MG

adults and children 12 years of age and over | 1 to 2 capsules
children 6 years to under 12 years of age | 1 capsule
children under 6 years of age | do not use this product in children under 6 years of age

50 MG

adults and children 12 years of age and over | 1 capsule
children 6 years to under 12 years of age | Ask a doctor, the proper dosage strength is not available in this package**

**Do not attempt to break capsules. The proper dosage strength and dosing information for children under 12 years of age is available on the 25 mg package.

Other Information

- Store at 20°C – 25°C (68°F – 77°F); excursions permitted to 15° – 30°C (59° – 86°F) [See USP Controlled Room Temperature]
- Protect from moisture
- Contains lactose

Inactive Ingredients

D&C Red #28, FD&C Blue #1, FD&C Red #40, Gelatin, Lactose and Starch.

Questions?

Questions or comments? (800) 616-2471

Distributed by

MAJOR® PHARMACEUTICALS
17177 N Laurel Park Drive, Suite 233,
Livonia, MI 48152